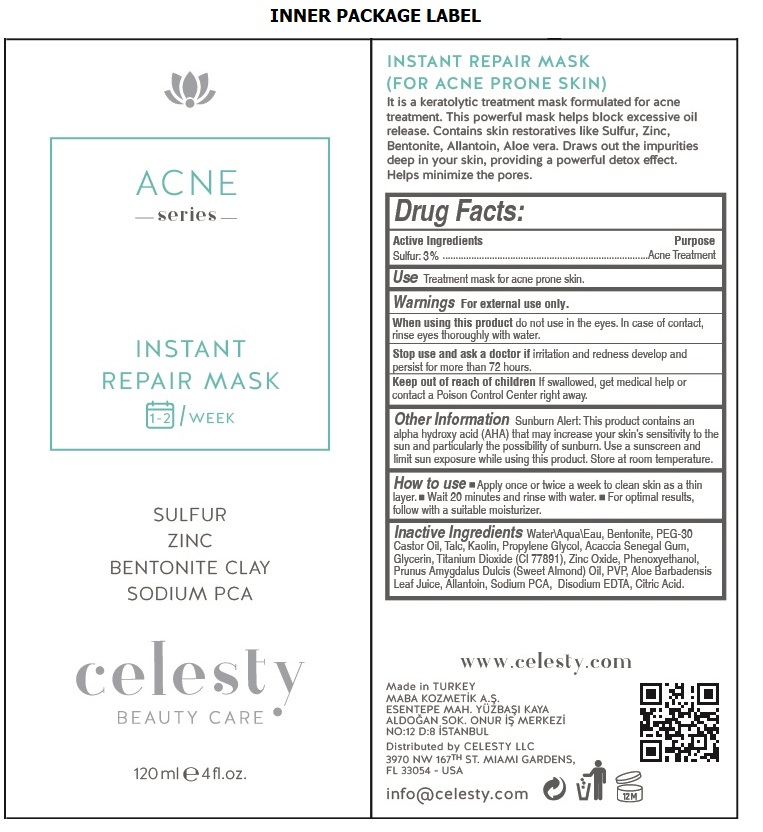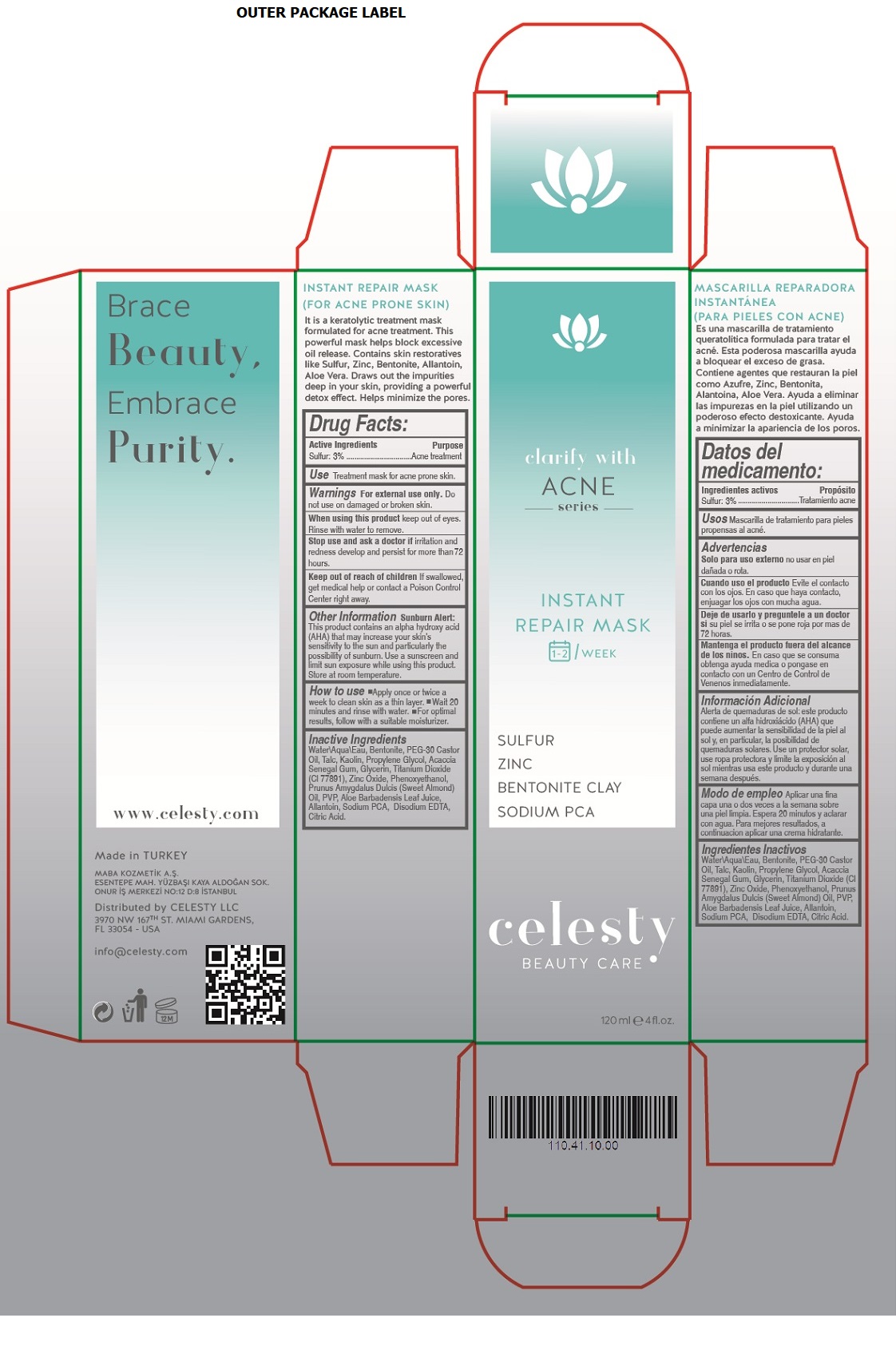 DRUG LABEL: Celesty
NDC: 81120-103 | Form: CREAM
Manufacturer: MABA KOZMETIK LIMITED SIRKETI
Category: otc | Type: HUMAN OTC DRUG LABEL
Date: 20201208

ACTIVE INGREDIENTS: SULFUR 3 g/100 mL
INACTIVE INGREDIENTS: WATER; BENTONITE; PEG-30 CASTOR OIL; TALC; KAOLIN; PROPYLENE GLYCOL; ACACIA; GLYCERIN; TITANIUM DIOXIDE; ZINC OXIDE; PHENOXYETHANOL; ALMOND OIL; POVIDONE, UNSPECIFIED; ALOE VERA LEAF; ALLANTOIN; SODIUM PYRROLIDONE CARBOXYLATE; EDETATE DISODIUM ANHYDROUS; CITRIC ACID MONOHYDRATE

celesty ACNE series INSTANT REPAIR MASK

Active Ingredients

Sulfur : 3%

Purpose

Acne treatment

Use

Treatment mask for acne prone skin.

Warnings

For external use only. Do not use on damaged or broken skin.

When using this product keep out of eyes. Rinse with water to remove.

Stop use and ask a doctor if irritation and redness develop and persist for more than 72 hours.

Keep out of reach of children If swallowed, get medical help or contact a Poison Control Center right away.

Other Information

Sunburn Alert: This product contains an alpha hydroxy acid (AHA) that may increase your skin's sensitivity to the sun and particularly the possibility of sunburn. Use a sunscreen and limit sun exposure while using this product. Store at room temperature.

How to use

• Apply once or twice a week to clean skin as a thin layer. • Wait 20 minutes and rinse with water. • For optimal results, follow with a suitable moisturizer.

Inactive Ingredients

Water\Aqua\Eau, Bentonite, PEG-30 Castor Oil, Talc, Kaolin, Propylene Glycol, Acaccia Senegal Gum, Glycerin, Titanium Dioxide (Cl 77891), Zinc Oxide, Phenoxyethanol, Prunus Amygdalus Dulcis (Sweet Almond) Oil, PVP, Aloe Barbadensis Leaf Juice, Allantoin, Sodium PCA, Disodium EDTA, Citric Acid.

clarify with ACNE series

1-2 / WEEK

SULFUR

ZINC

BENTONITE CLAY

SODIUM PCA

BEAUTY CARE

Brace Beauty, Embrace Purity.

www.celesty.com

Made in TURKEY

MABA KOZMETIK A.S.

ESENTEPE MAH. YUZBASI KAYA ALDOGAN SOK.

ONUR IS MERKEZI NO:12 D:8 ISTANBUL

Distributed by CELESTY LLC

3970 NW 167TH ST. MIAMI GARDENS,

FL 33054 - USA

info@celesty.com

(FOR ACNE PRONE SKIN)

It is a keratolytic treatment mask formulated for acne treatment. This powerful mask helps block excessive oil release. Contains skin restoratives like Sulfur, Zinc, Bentonite, Allantoin, Aloe vera. Draws out the impurities deep in your skin, providing a powerful detox effect. Helps minimize the pores.